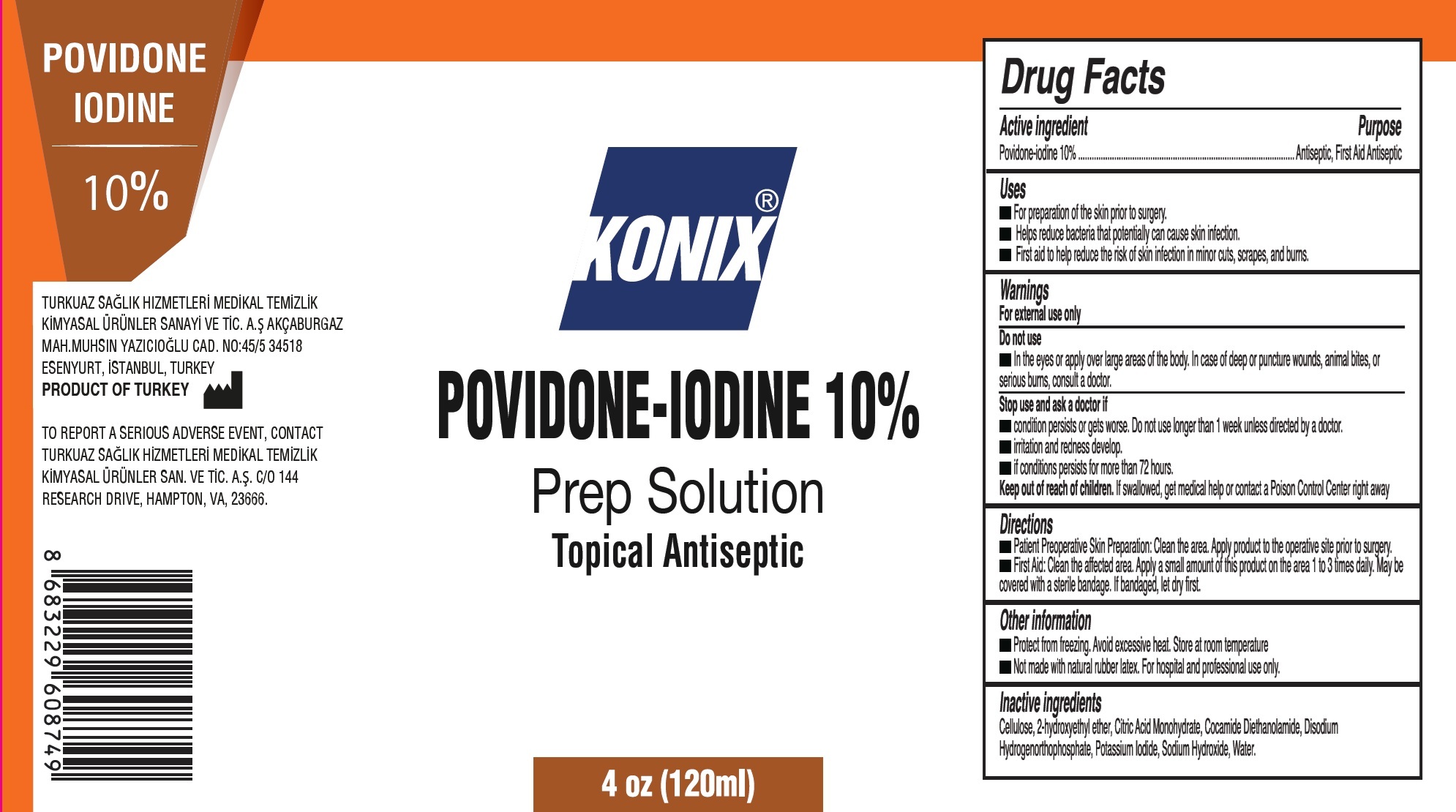 DRUG LABEL: Konix Povidone Iodine Topical Antiseptic
NDC: 73107-009 | Form: LIQUID
Manufacturer: TURKUAZ SAGLIK HIZMETLERI MEDIKAL TEMIZLIK KIMYASAL URUNLER SANAYI VE TICARET AS
Category: otc | Type: HUMAN OTC DRUG LABEL
Date: 20260219

ACTIVE INGREDIENTS: POVIDONE-IODINE 100 mg/1 mL
INACTIVE INGREDIENTS: POWDERED CELLULOSE; CITRIC ACID MONOHYDRATE; POTASSIUM IODIDE; SODIUM HYDROXIDE; WATER

Konix Povidone Iodine 10% Topical Antiseptic

Active ingredient

Povidone-iodine 10%

Purpose

Antiseptic, First Aid Antiseptic

Uses

- For preparation of the skin prior to surgery.
- Helps reduce bacteria that potentially can cause skin infection.
- First aid to help reduce the risk of skin infection in minor cuts, scrapes, and burns.

Warnings

For external use only

Do not use

- In the eyes or apply over large areas of the body. In case of deep or puncture wounds, animal bites, or serious burns, consult a doctor.

Stop use and ask a doctor if

- condition persists or gets worse. Do not use longer than 1 week unless directed by a doctor.
- irritation and redness develop.
- if conditions persists for more than 72 hours.

Keep out of reach of children.

If swallowed, get medical help or contact a Poison Control Center right away

Directions

- Patient Preperative Skin Preparation: Clean the area. Apply product to the operative site prior to sugery.
- First Aid:Clean the affected area. Apply a small amount of this product on the area 1 to 3 times daily. May be covered with a sterile bandage. If bandaged, let dry first.

Other information

- Protect from freezing. Avoid excessive heat. Store at room temperature
- Not made with natural rubber latex. For hospital and professional use only.

Inactive ingredients

Cellulose, 2-hydroxyethyl ether, Citric Acid Monohydrate, Cocamide Diethanolamide, Disodium Hydrogenorthophosphate, Potassium Iodide, Sodium Hydroxide, Water